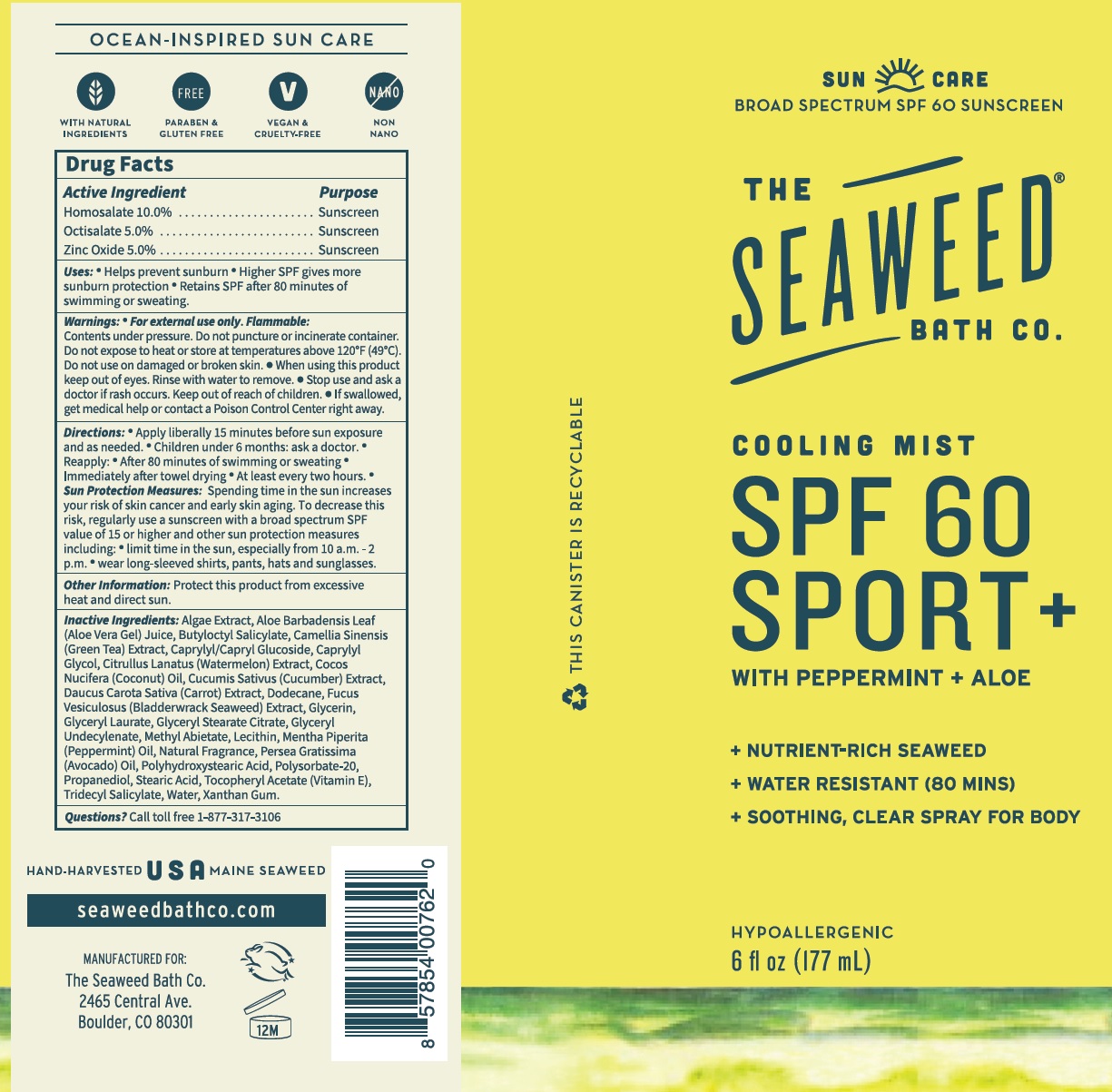 DRUG LABEL: SEAWEED BATH CO Cooling Mist SPF-60 Sport
NDC: 81159-258 | Form: LIQUID
Manufacturer: The Seaweed Bath Co.
Category: otc | Type: HUMAN OTC DRUG LABEL
Date: 20231111

ACTIVE INGREDIENTS: HOMOSALATE 100 mg/1 mL; OCTISALATE 50 mg/1 mL; ZINC OXIDE 50 mg/1 mL
INACTIVE INGREDIENTS: ALOE VERA LEAF; BUTYLOCTYL SALICYLATE; GREEN TEA LEAF; CAPRYLYL/CAPRYL OLIGOGLUCOSIDE; CAPRYLYL GLYCOL; WATERMELON; COCONUT OIL; CUCUMBER; CARROT; DODECANE; FUCUS VESICULOSUS; GLYCERIN; GLYCERYL LAURATE; GLYCERYL STEARATE CITRATE; GLYCERYL 1-UNDECYLENATE; METHYL ABIETATE; PEPPERMINT OIL; AVOCADO OIL; POLYSORBATE 20; PROPANEDIOL; STEARIC ACID; .ALPHA.-TOCOPHEROL ACETATE; TRIDECYL SALICYLATE; WATER; XANTHAN GUM

SEAWEED BATH CO. Cooling Mist SPF-60 Sport Spray

Active Ingredient

Homosalate 10.0%

Octisalate 5.0%

Zinc Oxide 5.0%

Purpose

Sunscreen

Uses:

- Helps prevent sunburn
- Higher SPF gives more sunburn protection
- Retains SPF after 80 minutes of swimming or sweating.

Warnings:

Contents under pressure. Do not punture or incinerate container. Do not expose to heat or store at temperatures above 120°F (49°C). For external use only. Flammable:

Do not use

on damaged or broken skin.

When using this product

- keep out of eyes. Rinse with water to remove.

Stop use and ask a doctor

ir rash occurs.

Keep out of reach of children.

- If swallowed, get medical help or contact a Poison Control Center right away.

Directions:

- Apply liberally 15 minutes before sun exposure and as needed.
- Children under 6 months: ask a doctor.
- Reapply:
- After 80 minutes of swimming or sweating
- Immediately after towel drying
- At least every two hours.
- Spending time in the sun increases your risk of skin cancer and early skin aging. To decrease this risk, regularly use a sunscreen with a broad spectrum SPF value of 15 or higher and other sun protection measures including: Sun Protection Measures:
- limit time in the sun, especially from 10 a.m. -2 p.m.
- wear long-sleeved shirts, pants, hats and sunglasses.

Other Information:

Protect this product from excessive heat and direct sun.

Inactive Ingredients:

Algae Extract, Aloe Barbadensis Leaf (Aloe Vera Gel) Juice, Butyloctyl Salicylate, Camellia Sinensis (Green Tea) Extract, Caprylyl/Capryl Glucoside, Caprylyl Glycol, Citrullus Lanatus (Watermelon) Extract, Cocos Nucifera (Coconut) Oil, Cucumis Sativus (Cucumber) Extract, Daucus Carota Sativa (Carrot) Extract, Dodecane, Fucus Vesiculosus (Bladderwrack Seaweed) Extract, Glycerin, Glyceryl Laurate, Glyceryl Stearate Citrate, Glyceryl Undecylenate, Methyl Abietate, Lecithin, Mentha Piperita (Peppermint) Oil, Natural Fragrance, Persea Gratissima (Avocado) Oil, Polyhydroxystearic Acid, Polysorbate-20, Propanediol, Stearic Acid, Tocopheryl Acetate (Vitamin E), Tridecyl Salicylate, Water, Xanthan Gum.

Questions?

Call toll free 1-877-317-3106